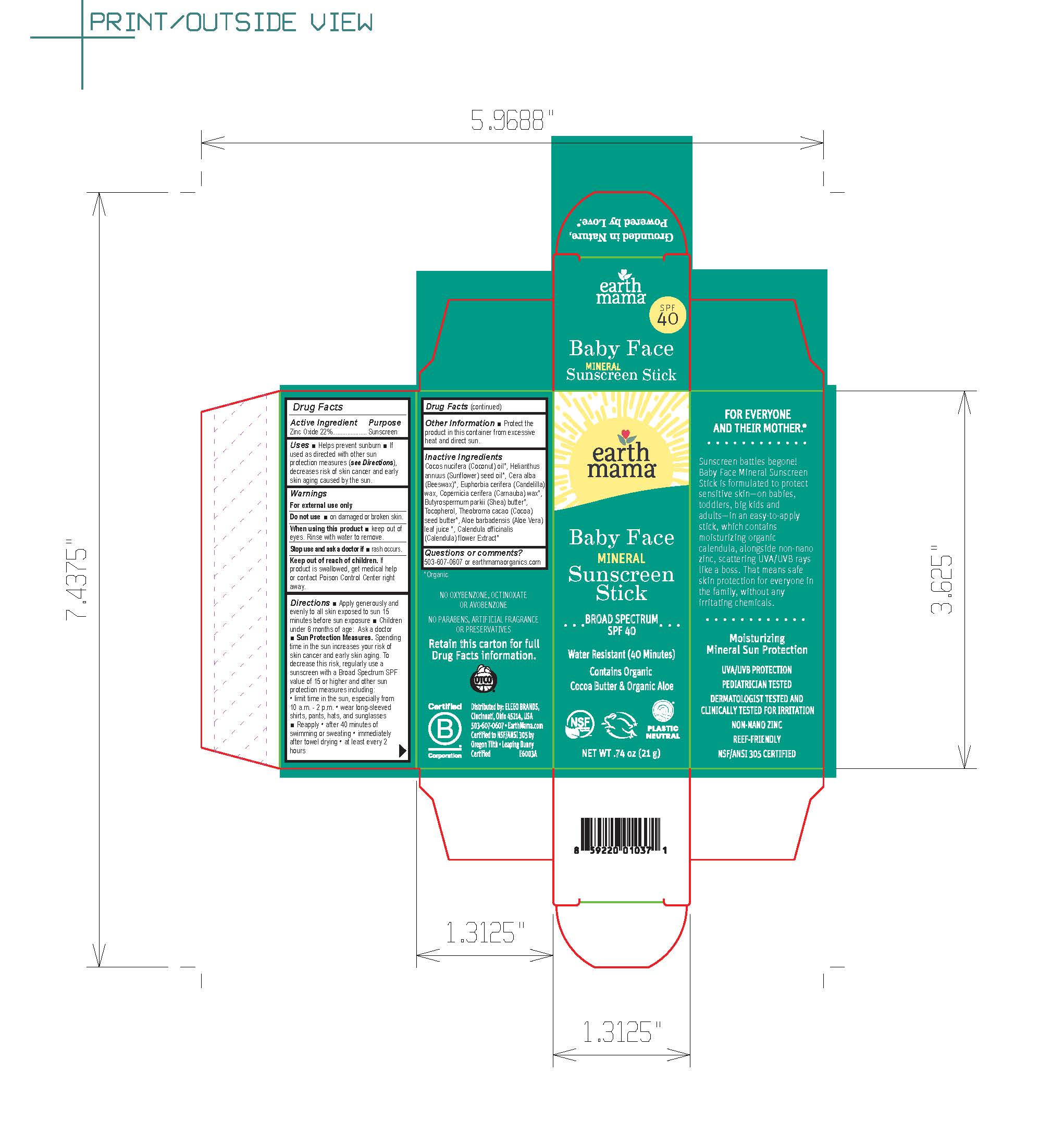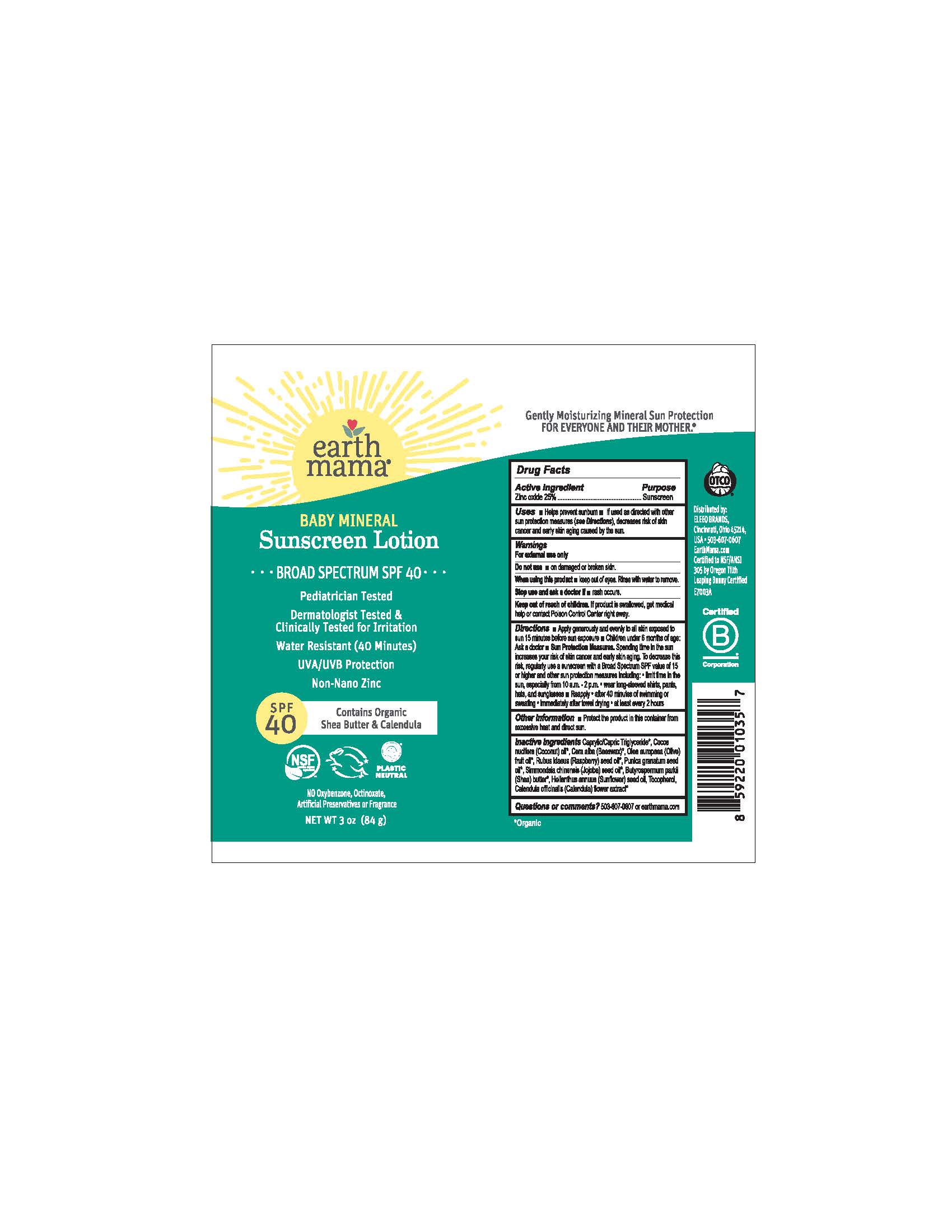 DRUG LABEL: Earth Mama Baby Face Mineral Sunscreen Stick SPF 40
NDC: 79747-143 | Form: STICK
Manufacturer: Eleeo Brands LLC
Category: otc | Type: HUMAN OTC DRUG LABEL
Date: 20250813

ACTIVE INGREDIENTS: ZINC OXIDE 220 mg/1 g
INACTIVE INGREDIENTS: COCONUT OIL; SUNFLOWER OIL; YELLOW WAX; CANDELILLA WAX; CARNAUBA WAX; SHEA BUTTER; TOCOPHEROL; COCOA BUTTER; ALOE VERA LEAF; CALENDULA OFFICINALIS FLOWER

Earth Mama Baby Face Mineral Sunscreen SPF 40

Active Ingredient

Zinc Oxide 22%

Purpose

Sunscreen

Uses

• Helps prevent sunburn • If used as directed with other sun protection measures (see Directions), decreases risk of skin cancer and early skin aging caused by the sun.

Warnings

For external use only

Do not use• on damaged or broken skin.

When using this product• keep out of eyes. Rinse with water to remove.

Stop use and ask a doctor if• rash occurs

Keep out of reach of children.If product is swallowed, get medical help or contact Poison Control Center right away.

Directions

• Apply generously and evenly to all skin exposed to sun 15 minutes before sun exposure • Children under 6 months of age: Ask a doctor
• Sun Protection Measures.Spending time in the sun increases your risk of skin cancer and early skin aging. To decrease this risk, regularly use a sunscreen with a Broad Spectrum SPF value of 15 or higher and other sun protection measures including: • limit time in the sun, especially from 10 a.m. - 2 p.m. • wear long-sleeved shirts, pants, hats, and sunglasses
• Reapply • after 40 minutes of swimming or sweating • immediately after towel drying • at least every 2 hours

Other Information

• Protect the product in this container from excessive heat and direct sun.

Inactive Ingredients

Cocos Nucifera (Coconut) Oil*, Helianthus Annuus (Sunflower) Seed Oil*, Cera Alba (Beeswax)*, Euphorbia Cerifera Cera (Candelilla) Wax, Copernicia Cerifera (Carnauba) Wax*, Butyrospermum Parkii (Shea) Butter*, Tocopherol, Theobroma Cacao (Cocoa) Seed Butter*, Aloe Barbadensis (Aloe Vera) Leaf Juice*, Calendula Officinalis (Calendula) Flower Extract*

*Organic

Questions or comments?

503-607-0607 or earthmamaorganics.com

FACE STICK

BROAD SPECTRUM SPF 40

Water Resistant (40 Minutes)

Contains Organic Cocoa Butter & Organic Aloe

PLASTIC NEUTRAL

NSF
contains organic ingredients

FOR EVERYONE AND THEIR MOTHER.®

Baby Face Mineral Sunscreen Stick is formulated to protect sensitive skin — on babies, toddlers, big kids and adults — without any irritating chemicals. Instead, it contains moisturizing organic calendula and aloe alongside non-nano zinc, which scatters UVA/UVB rays like a boss and helps provide safe skin protection for everyone in the family, in an easy-to-apply stick.

Moisturizing
Mineral Sun Protection

UVA/UVB Protection

PEDIATRICIAN TESTED

DERMATOLOGIST TESTED AND CLINICALLY TESTED FOR IRRITATION

NON-NANO ZINC

REEF FRIENDLY

NO OXYBENZONE, OCTINOXATE OR AVOBENZONE

NO PARABENS, ARTIFICIAL FRAGRANCE OR PRESERVATIVES

Retain this carton for full Drug Facts information.

Distributed by Eleeo Brands
Cincinnati, OH 456214 USA
Certified to NSF/ANSI 305 by Oregon Tilth
Leaping Bunny certified

no substantive label changes